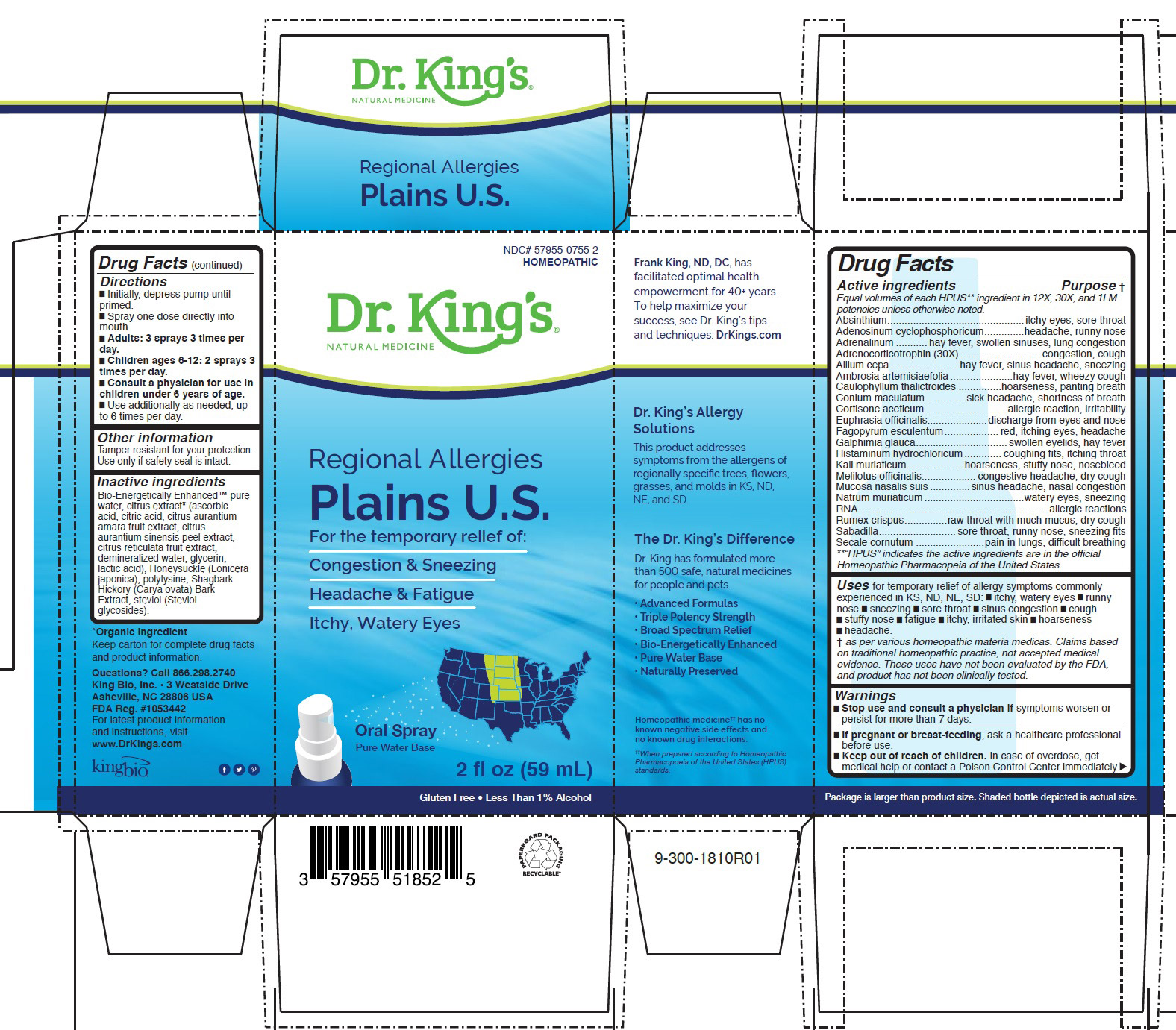 DRUG LABEL: Allergies Plains U.S.
NDC: 57955-0755 | Form: LIQUID
Manufacturer: King Bio Inc.
Category: homeopathic | Type: HUMAN OTC DRUG LABEL
Date: 20200708

ACTIVE INGREDIENTS: MELILOTUS OFFICINALIS TOP 12 [hp_X]/59 mL; WORMWOOD 12 [hp_X]/59 mL; ADENOSINE CYCLIC PHOSPHATE 12 [hp_X]/59 mL; EPINEPHRINE 12 [hp_X]/59 mL; CORTICOTROPIN 30 [hp_X]/59 mL; ONION 12 [hp_X]/59 mL; AMBROSIA ARTEMISIIFOLIA 12 [hp_X]/59 mL; CAULOPHYLLUM THALICTROIDES ROOT 12 [hp_X]/59 mL; CONIUM MACULATUM FLOWERING TOP 12 [hp_X]/59 mL; CORTISONE ACETATE 12 [hp_X]/59 mL; EUPHRASIA STRICTA 12 [hp_X]/59 mL; FAGOPYRUM ESCULENTUM 12 [hp_X]/59 mL; GALPHIMIA GLAUCA FLOWERING TOP 12 [hp_X]/59 mL; HISTAMINE DIHYDROCHLORIDE 12 [hp_X]/59 mL; POTASSIUM CHLORIDE 12 [hp_X]/59 mL; SUS SCROFA NASAL MUCOSA 12 [hp_X]/59 mL; SODIUM CHLORIDE 12 [hp_X]/59 mL; SACCHAROMYCES CEREVISIAE RNA 12 [hp_X]/59 mL; RUMEX CRISPUS ROOT 12 [hp_X]/59 mL; SCHOENOCAULON OFFICINALE SEED 12 [hp_X]/59 mL; CLAVICEPS PURPUREA SCLEROTIUM 12 [hp_X]/59 mL
INACTIVE INGREDIENTS: WATER; CARYA OVATA BARK; CITRUS BIOFLAVONOIDS; LONICERA JAPONICA FLOWER; POLYEPSILON-LYSINE (4000 MW); REBAUDIOSIDE A

Regional Allergies Plains U.S.

ACTIVE INGREDIENT

Drug Facts__________________________________________________________________________________________________________

HPUS active ingredients: Absinthium, Adenosinum cyclophosphoricum, Adrenalinum, Adrenocorticotrophin, Allium cepa, Ambrosia artemisiifolia, Caulophyllum thalictroides, Conium maculatum, Cortisone aceticum, Euphrasia officinalis, Fagopyrum esculentum, Galphimia glauca, Histaminum hydrochloricum, Kali muriaticum, Melilotus officinalis, Mucosa nasalis suis, Natrum muriaticum, RNA, Rumex crispus, Sabadilla and Secale cornutum. Equal volumes of each ingredient in 12X, 30X, and 1LM potencies.

INDICATIONS AND USAGE

Uses for temporary relief of allergy symptoms commonly
experienced in KS, ND, NE, SD: █ itchy, watery eyes █ runny
nose █ sneezing █ sore throat █ sinus congestion █ cough
█ stuffy nose █ fatigue █ itchy, irritated skin █ hoarseness
█ headache.

Inactive Ingredients:

Bio-Energetically Enhanced™ pure
water, citrus extract* (ascorbic
acid, citric acid, citrus aurantium
amara fruit extract, citrus
aurantium sinensis peel extract,
citrus reticulata fruit extract,
demineralized water, glycerin,
lactic acid), Honeysuckle (Lonicera
japonica), polylysine, Shagbark
Hickory (Carya ovata) Bark
Extract, steviol (Steviol
glycosides).

Warnings

- Stop use and consult a physician if symptoms worsen or
  persist for more than 7 days.

PREGNANCY OR BREAST FEEDING

If pregnant or breast-feeding, ask a healthcare professional
before use.

Keep out of reach of children. In case of overdose, get
medical help or contact a Poison Control Center immediately.

Directions

- Initially, depress pump until primed.
- Spray one dose directly into mouth.
- Adults: 3 sprays 3 times per day.
- Children ages 6-12: 2 sprays 3 times per day.
- Use additionally as needed, up to 6 times per day.

STORAGE AND HANDLING

Tamper resistant for your protection. Use only if seal is intact.

PURPOSE

Equal volumes of each HPUS** ingredient in 12X, 30X, and 1LM
potencies unless otherwise noted.
Absinthium................................................itchy eyes, sore throat
Adenosinum cyclophosphoricum..............headache, runny nose
Adrenalinum ...........hay fever, swollen sinuses, lung congestion
Adrenocorticotrophin (30X) ............................congestion, cough
Allium cepa........................hay fever, sinus headache, sneezing
Ambrosia artemisiaefolia......................hay fever, wheezy cough
Caulophyllum thalictroides ...............hoarseness, panting breath
Conium maculatum ............. sick headache, shortness of breath
Cortisone aceticum.............................allergic reaction, irritability
Euphrasia officinalis.....................discharge from eyes and nose
Fagopyrum esculentum...................red, itching eyes, headache
Galphimia glauca................................swollen eyelids, hay fever
Histaminum hydrochloricum............. coughing fits, itching throat
Kali muriaticum....................hoarseness, stuffy nose, nosebleed
Melilotus officinalis................... congestive headache, dry cough
Mucosa nasalis suis ..............sinus headache, nasal congestion
Natrum muriaticum...................................watery eyes, sneezing
RNA..................................................................allergic reactions
Rumex crispus...............raw throat with much mucus, dry cough
Sabadilla...........................sore throat, runny nose, sneezing fits
Secale cornutum ........................pain in lungs, difficult breathing
**“HPUS” indicates the active ingredients are in the official
Homeopathic Pharmacopeia of the United States.

Questions? Call 866.298.2740
King Bio, Inc. • 3 Westside Drive
Asheville, NC 28806 USA
FDA Reg. #1053442

For latest product information
and instructions, visit
www.DrKings.com